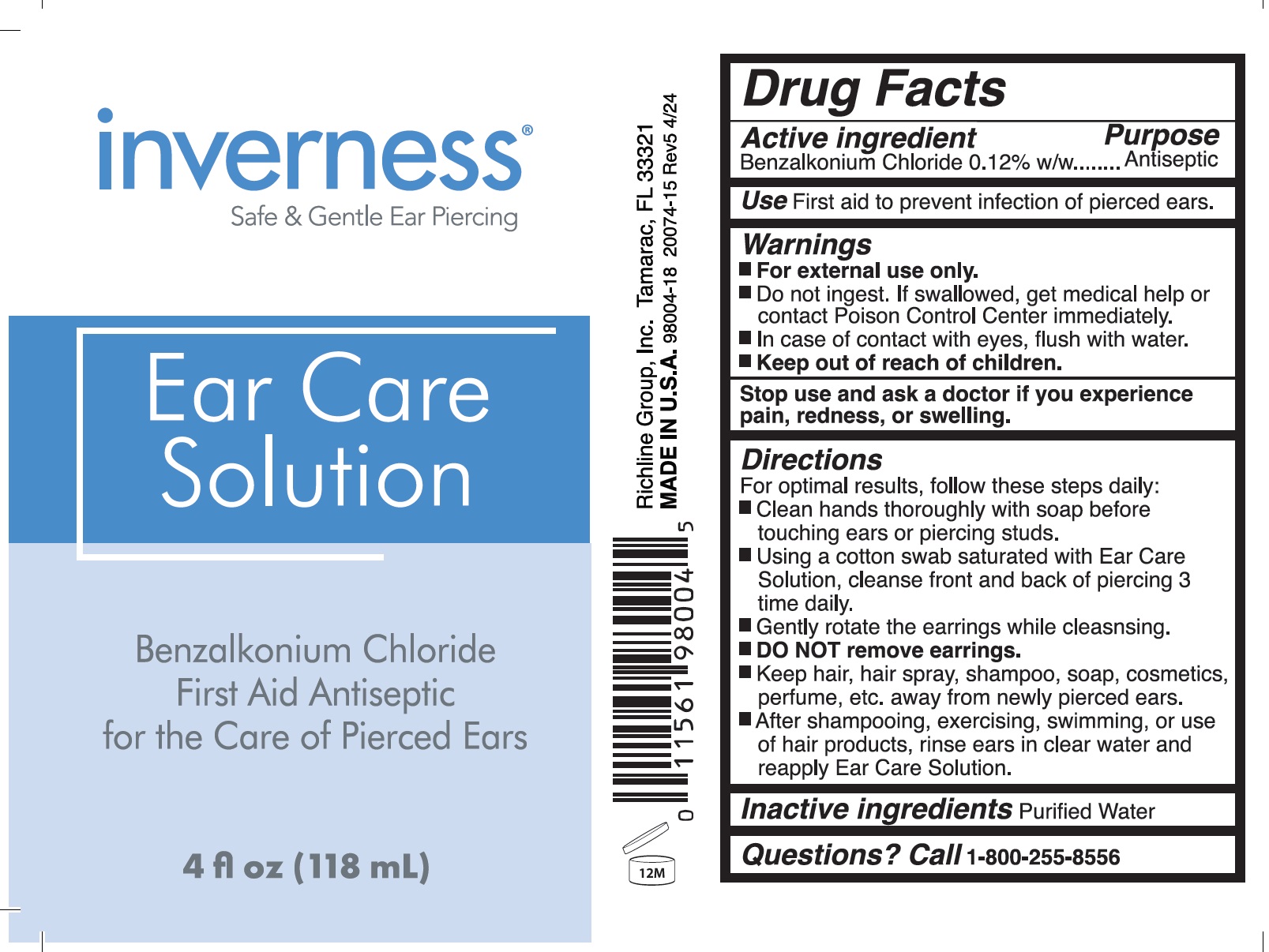 DRUG LABEL: Inverness Ear Care
NDC: 70094-007 | Form: SOLUTION
Manufacturer: The Richline Group, Inc.
Category: otc | Type: HUMAN OTC DRUG LABEL
Date: 20240509

ACTIVE INGREDIENTS: BENZALKONIUM CHLORIDE 1.2 mg/1 mL
INACTIVE INGREDIENTS: WATER

Inverness Ear Care Solution

Active ingredient

Benzalkonium Chloride 0.12% w/w

Purpose

Antiseptic

Use

First aid to prevent infection of pierced ears.

Warnings

- For external use only.
- Do not ingest. If swallowed, get medical help or contact Poison Control Center immediately.
- In case of contact with eyes, flush with water.

Stop use and ask a doctor if

you experience pain, redness, or swelling.

Directions

For optimal results, follow these steps daily:

- Clean hands thoroughly with soap before touching ears or piercing studs.
- Using a cotton swab saturated with Ear Care solution, cleanse front and back of piercing 3 time daily.
- Gently rotate the earrings while cleasnsing.
- DO NOT remove earrings.
- Keep hair, hair spray, shampoo, soap, cosmetics, perfume, etc. away from newly pierced ears.
- After shampooing, exercising, swimming, or use of hair products, rinse ears in clear water and reapply Ear Care Solution.

Inactive ingredients

Purified Water

Questions?

Call 1-800-255-8556